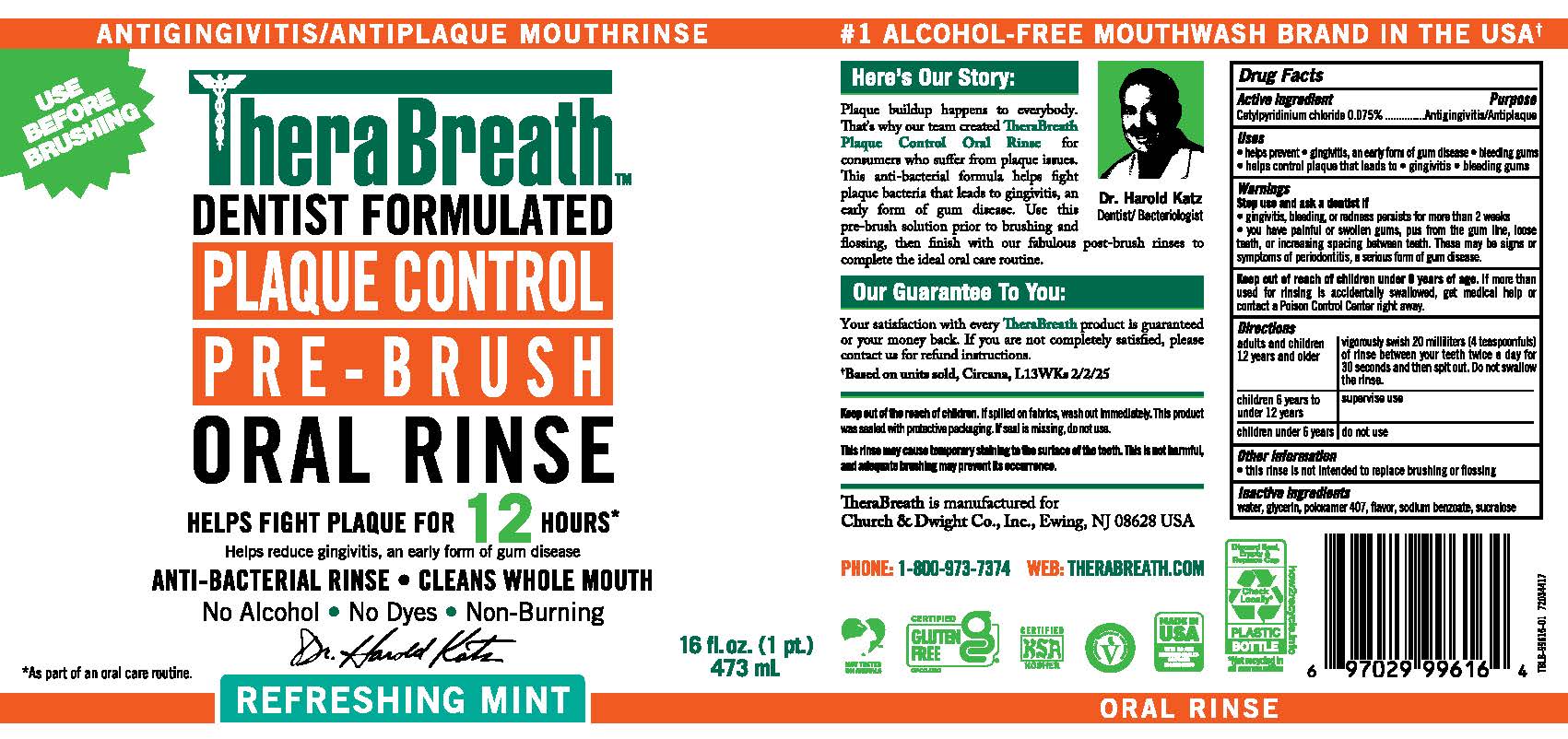 DRUG LABEL: Therabreath Plaque Control
NDC: 10237-259 | Form: RINSE
Manufacturer: Church & Dwight Co., Inc.
Category: otc | Type: HUMAN OTC DRUG LABEL
Date: 20251211

ACTIVE INGREDIENTS: CETYLPYRIDINIUM CHLORIDE 0.015 mg/20 mL
INACTIVE INGREDIENTS: WATER; GLYCERIN; POLOXAMER 407; SODIUM BENZOATE; SUCRALOSE

Therabreath™Plaque Control

Drug Facts

Active Ingredient

Cetylpyridinium Chloride 0.075%

Purpose

Antigingivitis/Antiplaque

Uses

- helps prevent • gingivitis, an early form of gum disease • bleeding gums
- helps control plaque that leads to • gingivitis • bleeding gums

Warnings

Stop use and ask a dentist if

- gingivitis, bleeding, or redness persists for more than 2 weeks
- you have painful or swollen gums, pus from the gum line, loose teeth, or increasing spacing between teeth. These may be signs or symptoms of periodontitis, a serious form of gum disease.

Keep out of reach of children under 6 years of age. If more than used for rinsing is accidentally swallowed, get medical help or contact a Poison Control Center right away.

Directions

adults and Children 12 years and older | vigorously swish 20 milliliters (4 teaspoonfuls) of rinse between your teeth twice a day for 30 seconds and then spit out. Do not swallow the rinse.
children 6 years to under 12 years | supervise use.
children under 6 years | do not use.

Other information

- this rinse is not intended to replace brushing or flossing

Inactive Ingredients

water, glycerin, poloxamer 407, flavor, sodium benzoate, sucralose

PRINCIPAL DISPLAY PANEL - 473 mL Bottle Label

USE BEFORE BRUSHING

ANTIGINGIVITIS/ANTIPLAQUE MOUTHRINSE

TheraBreath™

DENTIST FORMULATED

PLAQUE CONTROL

PRE-BRUSH

ORAL RINSE

HELPS FIGHT PLAQUE & GINGIVITIS FOR 12 HOURS*

Helps reduce gingivitis, an early form of gum disease

ANTI-BACTERIAL RINSE • CLEANS WHOLE MOUTH

No Alcohol • No Dyes • Non Burning

REFRESHING MINT

16 fl. oz.
473 mL

*As part of an oral care routine.